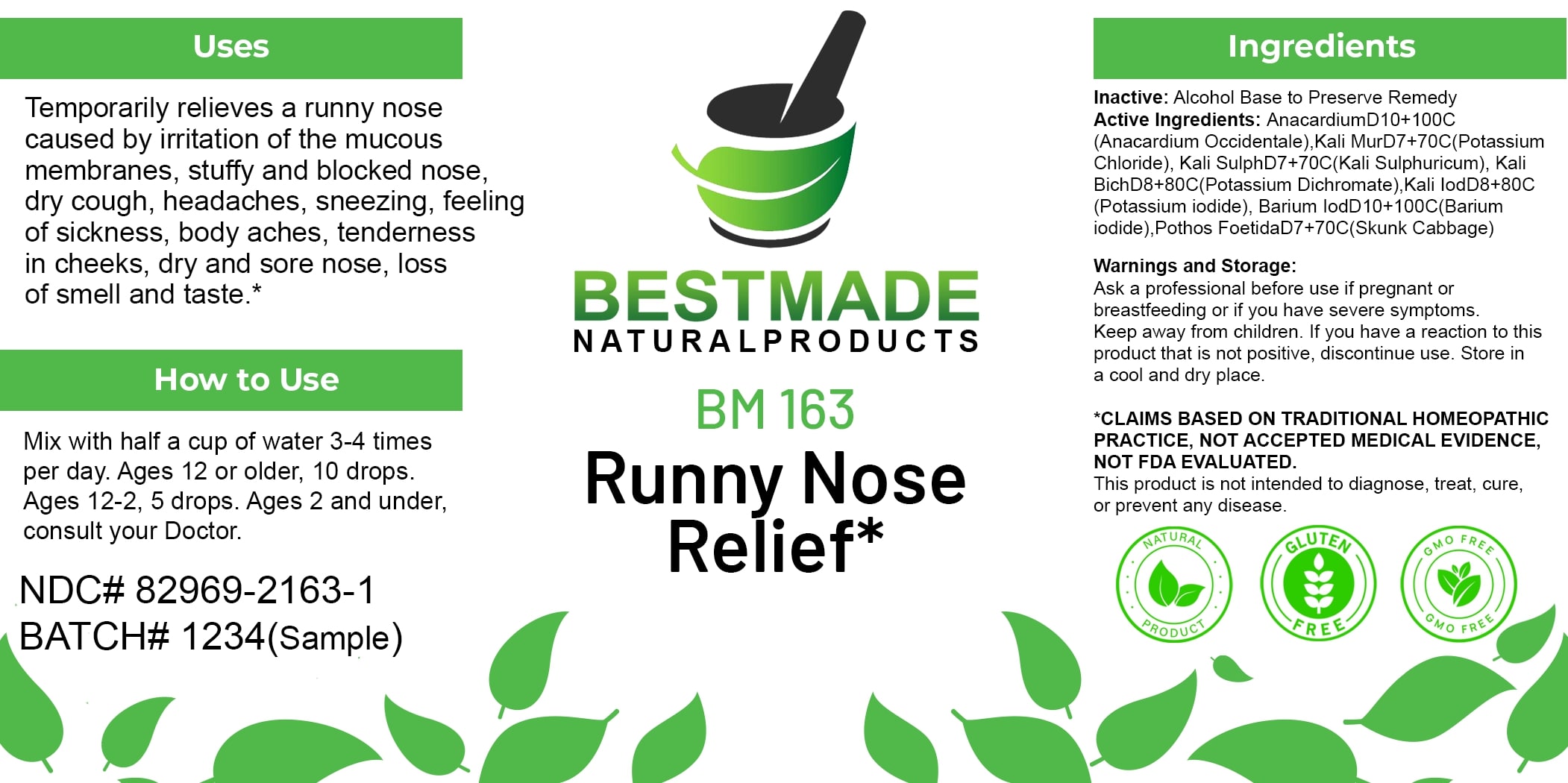 DRUG LABEL: Bestmade Natural Products BM163
NDC: 82969-2163 | Form: LIQUID
Manufacturer: Bestmade Natural Products
Category: homeopathic | Type: HUMAN OTC DRUG LABEL
Date: 20250218

ACTIVE INGREDIENTS: SYMPLOCARPUS FOETIDUS ROOT 30 [hp_C]/30 [hp_C]; POTASSIUM SULFATE 30 [hp_C]/30 [hp_C]; ANACARDIUM OCCIDENTALE FRUIT 30 [hp_C]/30 [hp_C]; POTASSIUM CHLORIDE 30 [hp_C]/30 [hp_C]; POTASSIUM IODIDE 30 [hp_C]/30 [hp_C]; BARIUM IODIDE 30 [hp_C]/30 [hp_C]; POTASSIUM DICHROMATE 30 [hp_C]/30 [hp_C]
INACTIVE INGREDIENTS: ALCOHOL 30 [hp_C]/30 [hp_C]

BM163

DOSAGE AND ADMINISTRATION

How to Use

Mix with half a cup of water 3-4 times per day. Ages 12 or older, 10 drops. Ages 12-2, 5 drops. Ages 2 and under, consult your Doctor.

INACTIVE INGREDIENT

Ingredients

Inactive: Alcohol Base to Preserve Remedy

ACTIVE INGREDIENT

Active Ingredients: AnacardiumD10+100C (Anacardium Occidentale), Kali MurD7+70C(Potassium Chloride), Kali SulphD7+70C(Kali Sulphuricum), Kali BichD6+60C(Potassium Dichromate), Kali Iod8+80C (Potassium Iodide), Banium IodD10+100C(Barium Iodide), Pothos FoetidaD7+70C(Skunk Cabbage)

Uses

Temporarily relieves a runny nose caused by irritation of the mucous membranes, stuffy and blocked nose, dry cough, headaches, sneezing, feeling of sickness, body aches, tenderness in cheeks, dry and sore nose, loss of smell and taste.*

*CLAIMS BASED ON TRADITIONAL HOMEOPATHIC PRACTICE, NOT ACCEPTED MEDICAL EVIDENCE. NOT FDA EVALUATED.

This product is not intended to diagnose, treat, cure, or prevent any disease.

Uses

Temporarily relieves a runny nose caused by irritation of the mucous membranes, stuffy and blocked nose, dry cough, headaches, sneezing, feeling of sickness, body aches, tenderness in cheeks, dry and sore nose, loss of smell and taste.*

*CLAIMS BASED ON TRADITIONAL HOMEOPATHIC PRACTICE, NOT ACCEPTED MEDICAL EVIDENCE. NOT FDA EVALUATED.

This product is not intended to diagnose, treat, cure, or prevent any disease.

KEEP OUT OF REACH OF CHILDREN

Warnings and Storage:

Ask a professional before use if pregnant or breastfeeding or if you have severe symptoms. Keep away from children. If you have a reaction to this product that is not positive, discontinue use. Store in a cool and dry place.

Warnings and Storage:

Ask a professional before use if pregnant or breastfeeding or if you have severe symptoms. Keep away from children. If you have a reaction to this product that is not positive, discontinue use. Store in a cool and dry place.

*CLAIMS BASED ON TRADITIONAL HOMEOPATHIC PRACTICE, NOT ACCEPTED MEDICAL EVIDENCE. NOT FDA EVALUATED.

This product is not intended to diagnose, treat, cure, or prevent any disease.

Entire package label